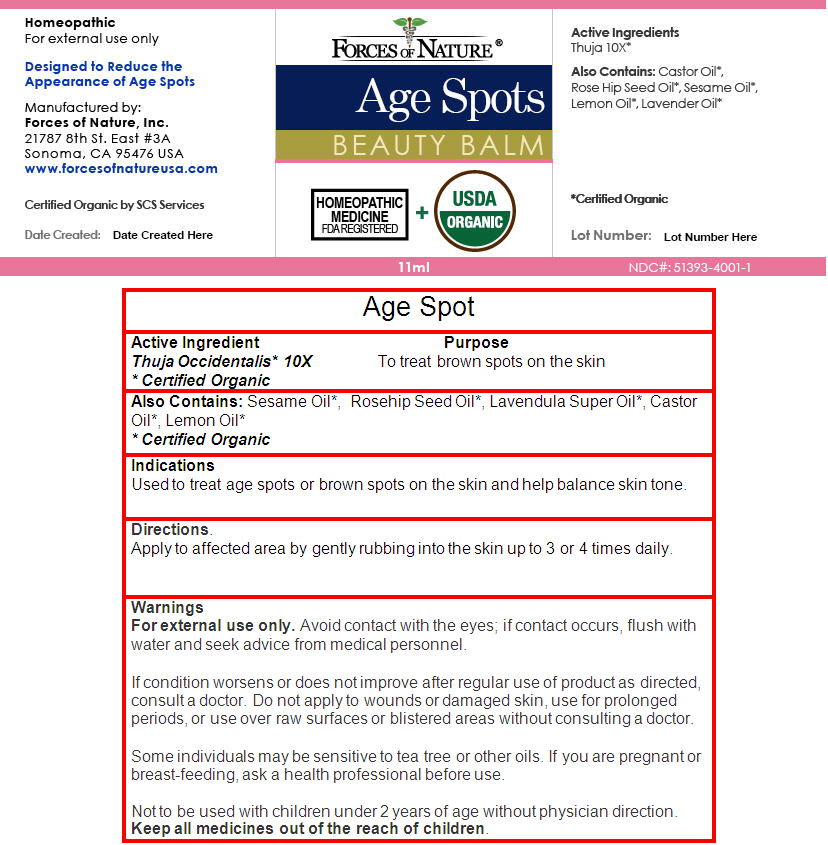 DRUG LABEL: Age Spot Control
NDC: 51393-4001 | Form: SOLUTION/ DROPS
Manufacturer: Forces of Nature
Category: homeopathic | Type: HUMAN OTC DRUG LABEL
Date: 20140102

ACTIVE INGREDIENTS: Thuja occidentalis leafy twig 10 [hp_X]/100 mL
INACTIVE INGREDIENTS: Sesame Oil; Rosa Moschata Oil; Lavandula Angustifolia Flower; Castor Oil; Lemon Oil

Age Spot Control

Active Ingredient

Thuja Occidentalis [Certified Organic] 10X

Purpose

To treat brown spots on the skin

Also Contains

Sesame Oil [Certified Organic] , Rosehip Seed Oil, Lavendula Super Oil, Castor Oil, Lemon Oil

Indications

Used to treat age spots or brown spots on the skin and help balance skin tone.

Directions

Apply to affected area by gently rubbing into the skin up to 3 or 4 times daily.

Warnings

For external use only. Avoid contact with the eyes; if contact occurs, flush with water and seek advice from medical personnel.

ASK DOCTOR

If condition worsens or does not improve after regular use of product as directed, consult a doctor. Do not apply to wounds or damaged skin, use for prolonged periods, or use over raw surfaces or blistered areas without consulting a doctor.

Some individuals may be sensitive to tea tree or other oils.

PREGNANCY OR BREAST FEEDING

If you are pregnant or breast-feeding, ask a health professional before use.

DO NOT USE

Not to be used with children under 2 years of age without physician direction.

KEEP OUT OF REACH OF CHILDREN

Keep all medicines out of the reach of children.

Manufactured by:
Forces of Nature, Inc.
21787 8th St. East #3A
Sonoma, CA 95476 USA

PRINCIPAL DISPLAY PANEL - 11 mL Bottle Label

FORCES OF NATURE ®

Age Spots
BEAUTY BALM

HOMEOPATHIC
MEDICINE
FDA REGISTERED
+
USDA
ORGANIC

11ml